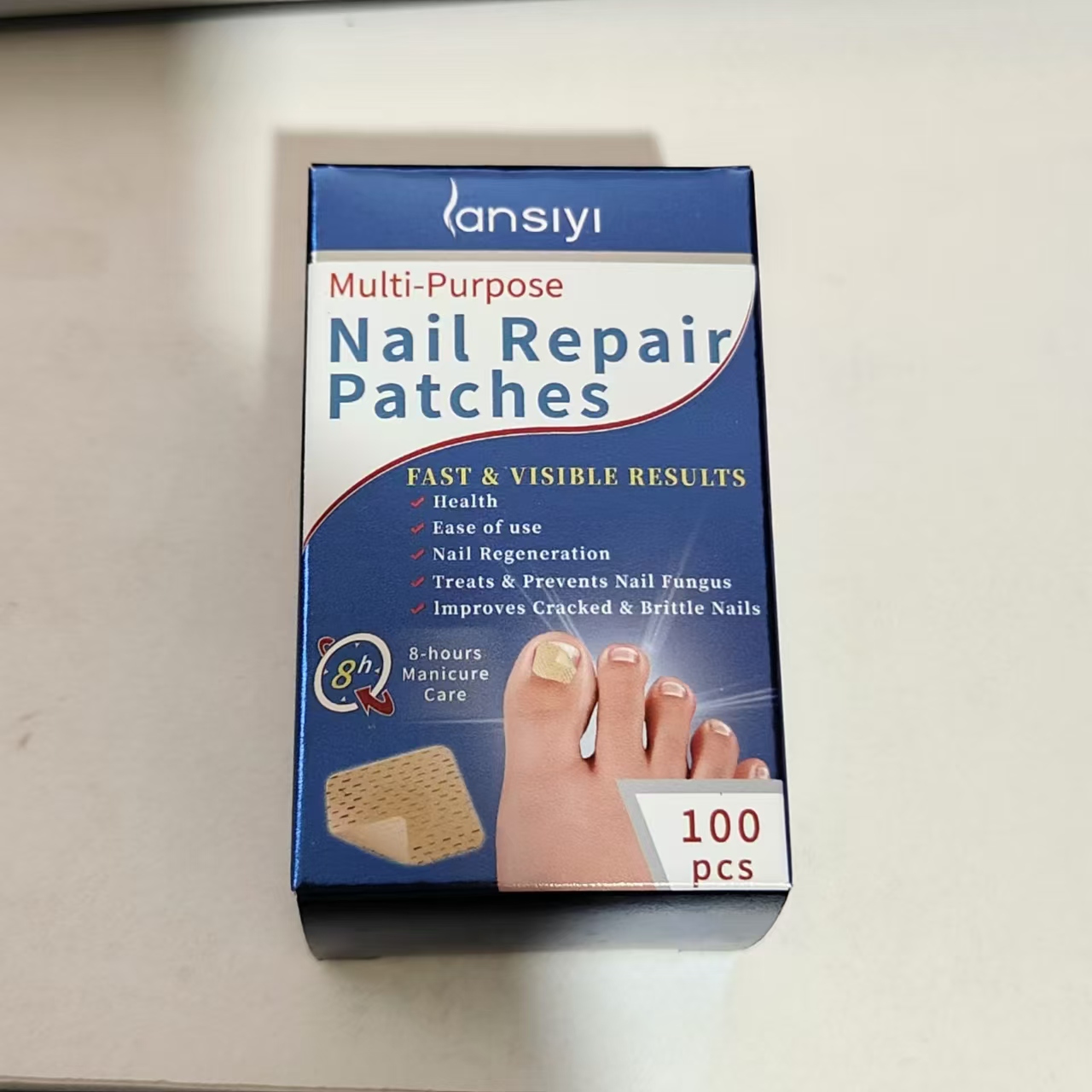 DRUG LABEL: Nail Repair Patches
NDC: 84727-002 | Form: OINTMENT
Manufacturer: Guangzhou Baishili Trading Co., Ltd
Category: otc | Type: HUMAN OTC DRUG LABEL
Date: 20240917

ACTIVE INGREDIENTS: ALLANTOIN 100 mg/5 g; TEA TREE OIL 100 mg/5 g; GARLIC 100 mg/5 g
INACTIVE INGREDIENTS: GLYCERIN 100 mg/5 g

Active Ingredient

Tea tree oil 20%

Allantoin 5%

Garlic Extract 0.8%

Usage

Remove the protective paper from the patch and apply it to the affected area by pressingfirmly.

Usage

Remove the protective paper from thepatch and apply it to the affected area by pressingfirmly.

Warning

External and personal use only- do notshare.Avoid contact with eves. lf irritation occursdiscontinue use.Do not use if you are hyperse.nsitive to any of the ingredients,

Stop use and ask a doctor if

Do not use if you are hyperse-nsitive to any of the ingredients.

Warning

External and personal use only- do notshare.Avoid contact with eyes. lf irritation occursdiscontinue use.Do not use if you are hyperse-nsitive to any of the ingredients.

Warning

External and personal use only- do notshare.Avoid contact with eyes.lf irritation occursdiscontinue use.Do not use if you are hyperse.nsitive to any of the ingredients

DOSAGE & ADMINISTRATION SECTION

Stick one on each nail, and stick each piece for 8 hours

Inactive Ingredients

Glycerin,Kochia, Conidium